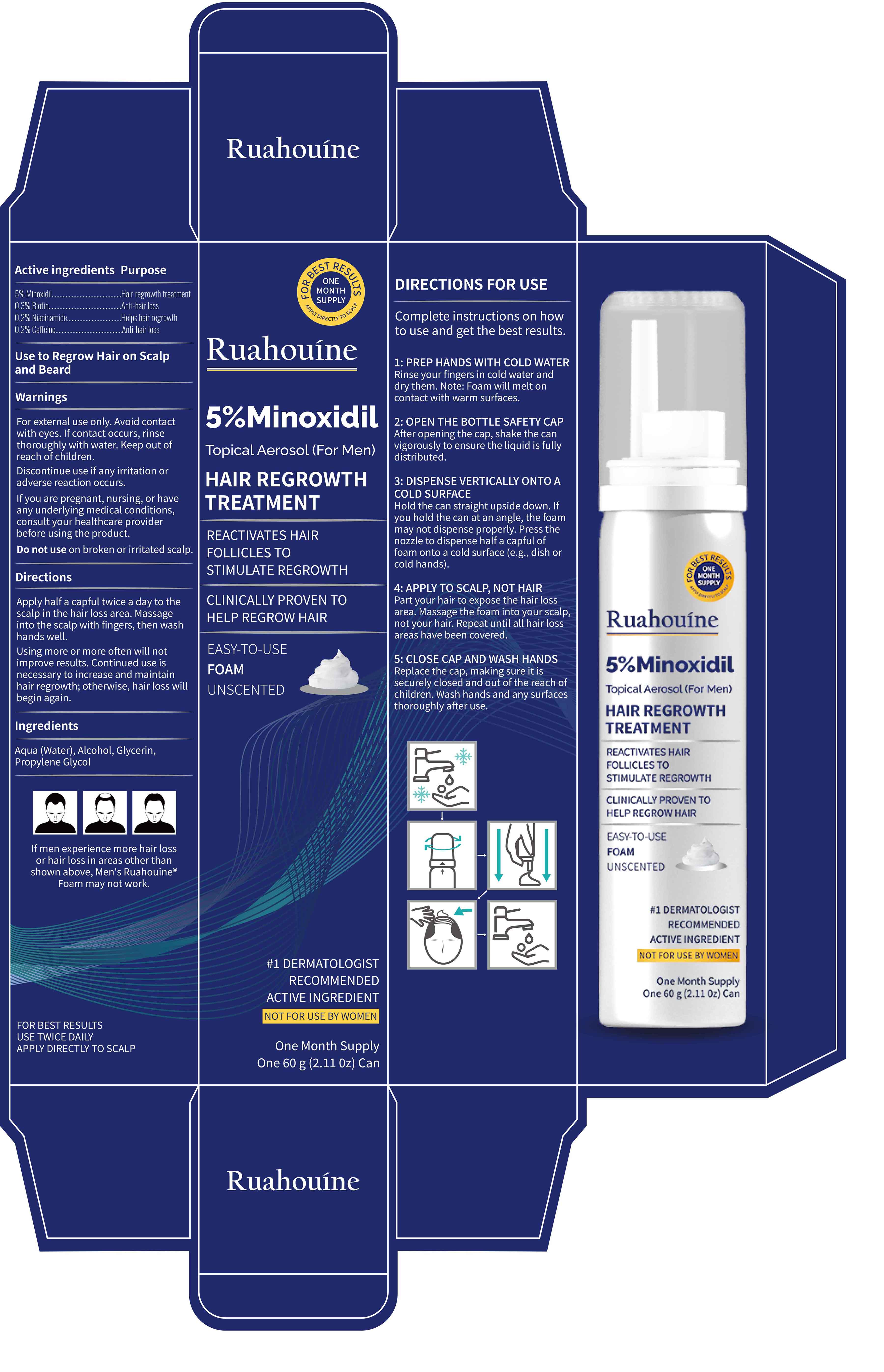 DRUG LABEL: 5% Minoxidil Topical Aerosol(For Men)
NDC: 84355-005 | Form: AEROSOL, FOAM
Manufacturer: Guangzhou Binsi Clothing Co.,Ltd.
Category: otc | Type: HUMAN OTC DRUG LABEL
Date: 20250514

ACTIVE INGREDIENTS: MINOXIDIL 5 g/100 g; CAFFEINE 0.2 g/100 g; NIACINAMIDE 0.2 g/100 g; BIOTIN 0.3 g/100 g
INACTIVE INGREDIENTS: GLYCERIN; PROPYLENE GLYCOL; AQUA; ALCOHOL

5% Minoxidil Topical Aerosol

ACTIVE INGREDIENT

Minoxidil 5%
Biotin 0.3%
Niacinamide 0.2%
Caffeine 0.2%

PURPOSE

Hair regrowth treatment
Anti-hair loss
Helps hair regrowth
Anti-hair loss

INDICATIONS AND USAGE

Use to Regrow Hair on Scalpand Beard

WARNINGS

For external use only.

Do not use on broken or irritated scalp

WHEN USING

Avoid contactwith eyes.
If you are pregnant, nursing, or haveany underlying medical conditions,consult your healthcare providerbefore using the product.

Discontinue use if any irritation oradverse reaction occurs.

Keep out ofreach of children.

DOSAGE AND ADMINISTRATION

Apply half a capful twice a day to thescalp in the hair loss area. Massageinto the scalp with fingers, then washhands well.
Using more or more often will notimprove results. Continued use isnecessary to increase and maintainhair regrowth, otherwise, hair loss willbegin again.
Complete instructions on howto use and get the best results.
1: PREP HANDS WITH COLD WATERRinse your fingers in cold water anddry them. Note: Foam will melt oncontact with warm surfaces
2: OPEN THE BOTTLE SAFETY CAPAfter opening the cap, shake the canvigorously to ensure the liquid is fullydistributed.
3: DISPENSE VERTICALLY ONTO ACOLD SURFACEHold the can straight upside down. lfyou hold the can at an angle, the foammay not dispense properly. Press thenozzle to dispense half a capful offoam onto a cold surface (e.g., dish orcold hands).
4: APPLY TO SCALP, NOT HAIRPart your hair to expose the hair lossarea. Massage the foam into your scalp,not your hair. Repeat until all hair lossareas have been covered.
5: CLOSE CAP AND WASH HANDSReplace the cap, making sure it issecurely closed and out of the reach ofchildren. Wash hands and any surfacesthoroughly after use.

INACTIVE INGREDIENT

Aqua (Water)
Alcohol
Glycerin
Propylene Glycol